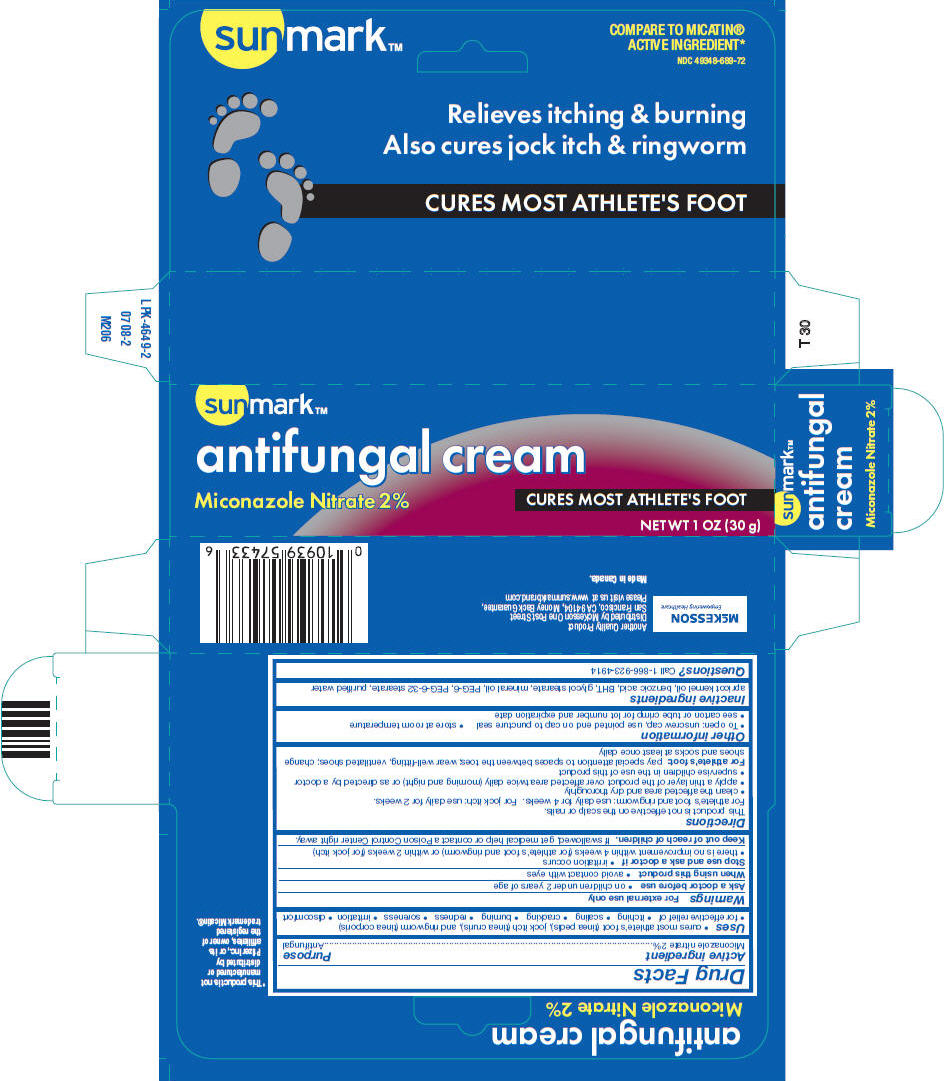 DRUG LABEL: SUNMARK MICONAZOLE NITRATE

NDC: 49348-689 | Form: CREAM
Manufacturer: Strategic Sourcing Services LLC
Category: otc | Type: HUMAN OTC DRUG LABEL
Date: 20250730

ACTIVE INGREDIENTS: MICONAZOLE NITRATE 20 mg/1 g
INACTIVE INGREDIENTS: APRICOT KERNEL OIL; BENZOIC ACID; BUTYLATED HYDROXYTOLUENE; GLYCOL STEARATE; MINERAL OIL; POLYETHYLENE GLYCOL 300; WATER

sunmark™
antifungal

Drug Facts

Active ingredient

Miconazole nitrate 2%

Purpose

Antifungal

Uses

- cures most athlete's foot (tinea pedis), jock itch (tinea cruris), and ringworm (tinea corporis)
- for effective relief of
  - itching
  - scaling
  - cracking
  - burning
  - redness
  - soreness
  - irritation
  - discomfort

Warnings

For external use only

Ask a doctor before use

- on children under 2 years of age

When using this product

- avoid contact with eyes

Stop use and ask a doctor if

- irritation occurs
- there is no improvement within 4 weeks (for athlete's foot and ringworm) or within 2 weeks (for jock itch)

Keep out of reach of children.If swallowed, get medical help or contact a Poison Control Center right away.

Directions

This product is not effective on the scalp or nails.

For athlete's foot and ringworm: use daily for 4 weeks. For jock itch: use daily for 2 weeks.

- clean the affected area and dry thoroughly
- apply a thin layer of the product over affected area twice daily (morning and night) or as directed by a doctor
- supervise children in the use of this product

For athlete's foot:pay special attention to spaces between the toes; wear well-fitting, ventilated shoes; change shoes and socks at least once daily

Other information

- To open: unscrew cap, use pointed end on cap to puncture seal
- store at room temperature
- see carton or tube crimp for lot number and expiration date

Inactive ingredients

apricot kernel oil, benzoic acid, BHT, glycol stearate, mineral oil, PEG-6, PEG-6-32 stearate, purified water

Questions?

Call 1-866-923-4914

Distributed by McKesson One Post Street
San Francisco, CA 94104

PRINCIPAL DISPLAY PANEL - 30 g Tube Carton

sunmark™

antifungal cream

Miconazole Nitrate 2%
CURES MOST ATHLETE'S FOOT

NET WT 1 OZ (30 g)